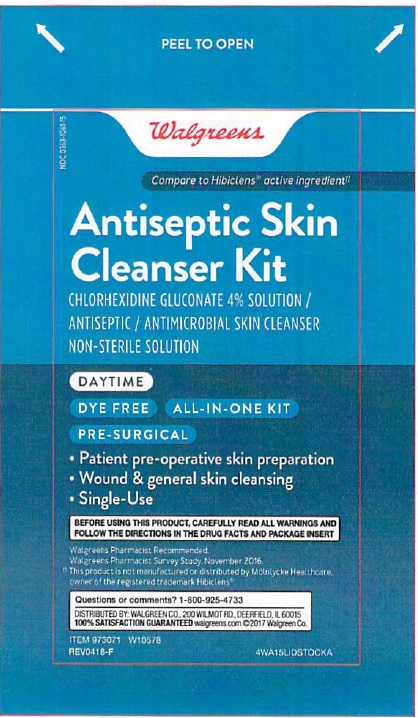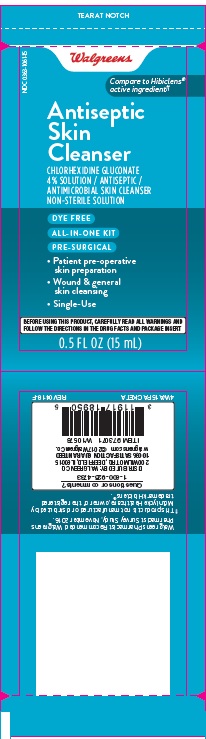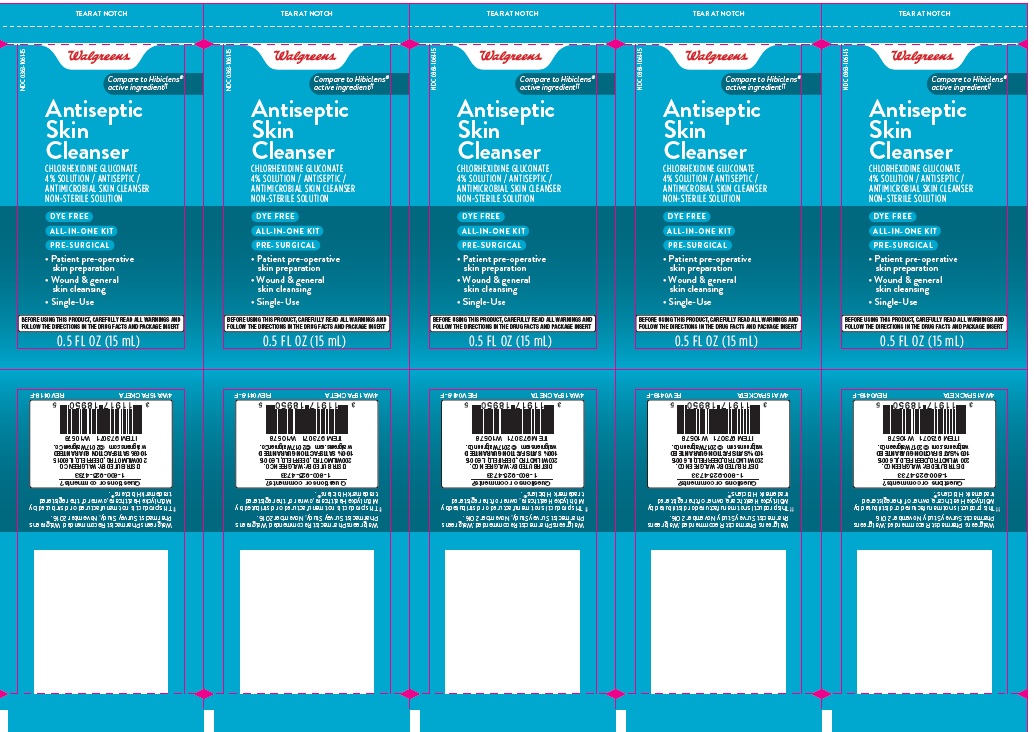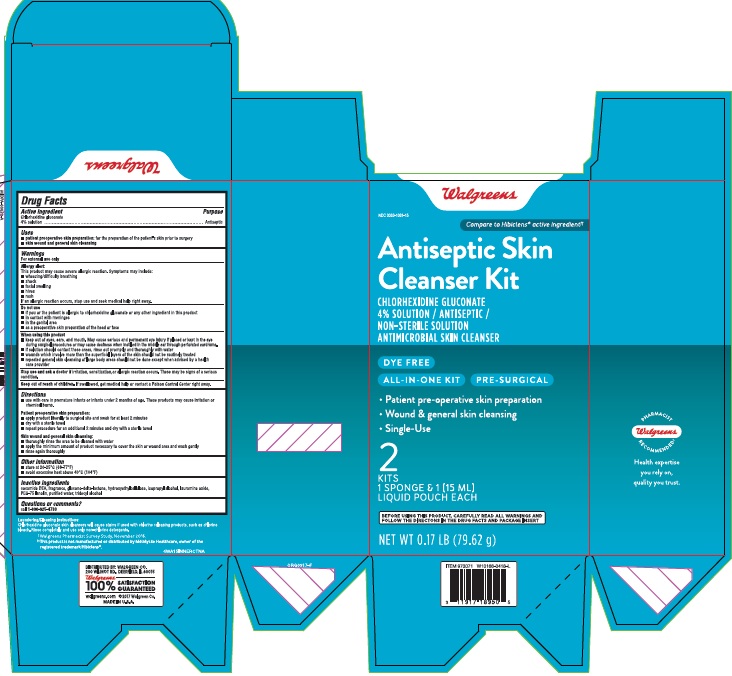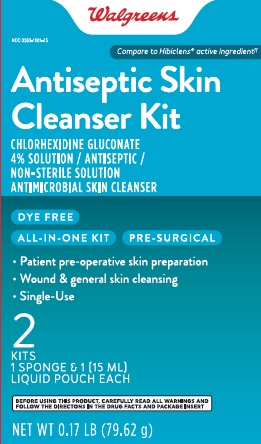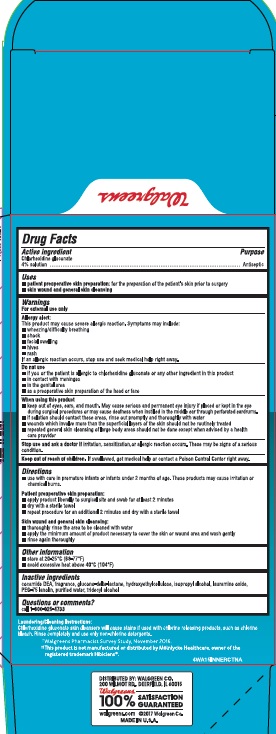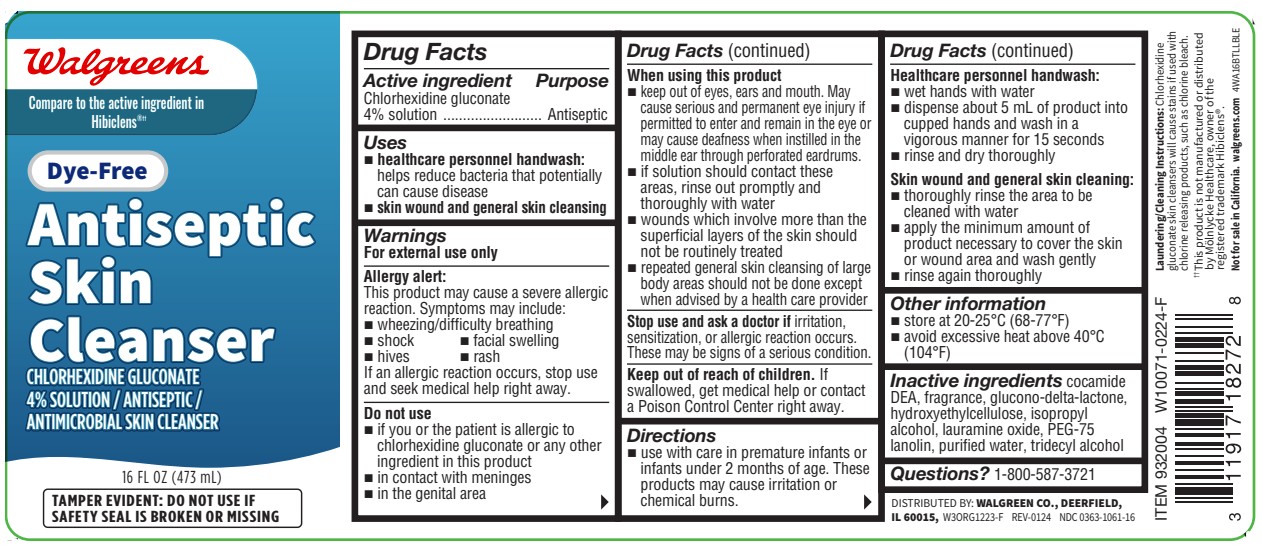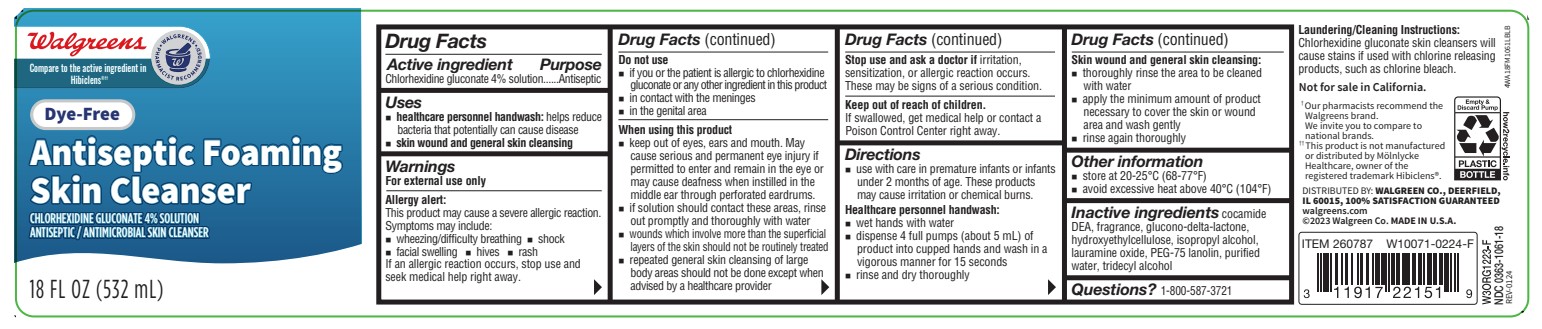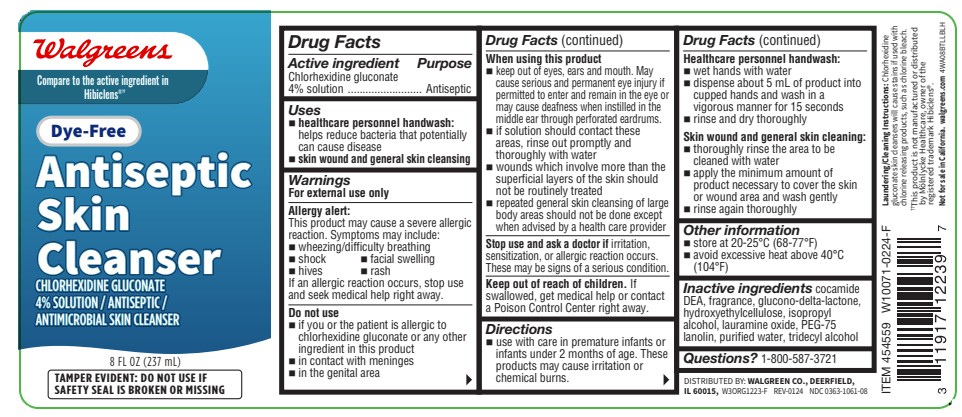 DRUG LABEL: Antiseptic Skin Cleanser
NDC: 0116-0161 | Form: LIQUID
Manufacturer: Xttrium Laboratories, Inc.
Category: otc | Type: HUMAN OTC DRUG LABEL
Date: 20250430

ACTIVE INGREDIENTS: CHLORHEXIDINE GLUCONATE 4 mg/100 mL
INACTIVE INGREDIENTS: LAURAMINE OXIDE; COCO DIETHANOLAMIDE; PEG-75 LANOLIN; HYDROXYETHYL CELLULOSE (2000 CPS AT 1%); ISOPROPYL ALCOHOL; WATER; TRIDECYL ALCOHOL; GLUCONOLACTONE

Walgreens 4% CHG

Active Ingredient

Chlorhexidine gluconate 4% Solution

Purpose

Antiseptic

Uses

- healthcare personnel handwash: helps reduce bacteria that potentially can cause disease
- skin wound and general skin cleansing

Warnings

For external use only

Allergy alert:

This product may cause a severe allergic reaction. Symptoms may include:

- wheezing/difficulty breathing
- facial swelling
- hives
- rash

If an allergic reaction occurs, stop use and seek medical help right away.

Do not use

- if you or the patient is allergic to chlorhexidine gluconate or any other ingredient in this product
- in contact with meninges
- in the genital area

When using this product

- keep out of eyes, ears, and mouth. May cause serious and permanent eye injury if pemitted to ener and remain in the eye or may cause deafness when instilled in the middle eat through perforated eardrums..
- if solution should contact these areas, rinse out promptly and thoroughly with water
- wounds which involve more than the superficial layers of the skin should not be routinely treated
- repeated general skin cleansing of large body areas should not be done except when advised by a health care provider

Stop use and ask a doctor if

irritation, sensitization, or allergic reaction occurs. These may be signs of a serious condition.

Keep out of reach of children.

If swallowed, get medical help or contact a Poison Control Center right away.

Directions

- use with care in premature infants or infants under 2 months of age. These products may cause irritation or chemical burns.

Healthcare personnel handwash:

- wet hands with water
- dispense about 5 mL of product into cupped hands and wash in a vigorous manner for about 15 seconds
- rinse and dry thoroughly

Skin wound and normal skin cleansing:

- thoroughly rinse the area to be cleaned with water
- apply the minimum amount of product necessary to cover the skin or wound area and wash gently
- rinse again thoroughly

Other information

- store at 20-25° C (68-77°F)
- avoid excessive heat above 40°C (104°F)

Inactive ingredients

cocamide DEA, fragrance, glucono-delta-lactone, hydroxyethylcellulose, isopropyl alcohol, lauramine oxide, PEG-75 lanolin, purified water, tridecyl alcohol.

Questions?

1-800-587-3721

OTHER SAFETY INFORMATION

Laundering/Cleaning Instructions: Chlorhexidine gluconate skin cleansers will cause stains if used with chlorine-releasing products. Rinse completely and use only non-chlorine detergents.

WARNING: This product contains a chemical (cocamide DEA) known to the State of California to cause cancer.

‡Walgreens Pharmacist Survey Study, November 2014

‡‡This product is not manufactured or distributed by Mölnlycke Healthcare, owner of the registered trademark Hibiclens®.

Distributed by: Walgreen Co.

200 Wilmot RD., Deerfield, IL 60015

100% Satisfaction Guaranteed

walgreens.com

©2015 Walgreen Co. Made in USA

RECENT MAJOR CHANGES

Surgical handscrub removed

Package label and principal display panel

Walgreens

Compare to the Hibiclens® active ingredient

NDC 0363-1061-08

Dye-Free

Antiseptic Skin Cleanser

CHLORHEXIDINE GLUCONATE 4% SOLUTION / ANTISEPTIC / ANTIMICROBIAL SKIN CLEANSER

DYE FREE

TAMPER EVIDENT: DO NOT USE IF SAFETY SEAL IS BROKEN OR MISSING

8 FL OZ (237 mL)

NDC 0363-1061-18

Walgreens

Compare to Hibiclens® active ingredient

Dye-Free Antiseptic Skin Cleanser

CHLORHEXIDINE GLUCONATE 4% SOLUTION / ANTISEPTIC / ANTIMICROBIAL SKIN CLEANSER

TAMPER EVIDENT: DO NOT USE IF SAFETY SEAL IS BROKEN OR MISSING

18 FL OZ (532 mL)

NDC 0363-1061-16

Walgreens

Compare to Hibiclens® active ingredient

Dye-Free Antiseptic Skin Cleanser

CHLORHEXIDINE GLUCONATE 4% SOLUTION / ANTISEPTIC / ANTIMICROBIAL SKIN CLEANSER

TAMPER EVIDENT: DO NOT USE IF SAFETY SEAL IS BROKEN OR MISSING

16 FL OZ (473 mL)

Carton

NDC 0363-1061-15

Walgreens, Co.

Chlorhexidine Gluconate 4% Solution

Antiseptic Skin Cleansing Kit

Distributed by:

Xttrium Laboratories, Inc.,

Mount Prospect, IL 60056

4WAL15INNERCTNA

0.5 FL OZ (15 mL)

Lidstock

NDC 0363-1061-15

Walgreens, Co.

Chlorhexidine Gluconate 4% Solution

Antiseptic Skin Cleansing Kit

Distributed by:

Xttrium Laboratories, Inc.,

Mount Prospect, IL 60056

4WAL15LIDSTOCKA

0.5 FL OZ (15 mL)

Packet

NDC 0363-1061-15

Walgreens, Co.

Chlorhexidine Gluconate 4% Solution

Antiseptic Skin Cleansing Convenience Kit

Distributed by:

Xttrium Laboratories, Inc.,

Mount Prospect, IL 60056

4WAL15PACKETA
0.5 FL OZ (15 mL)